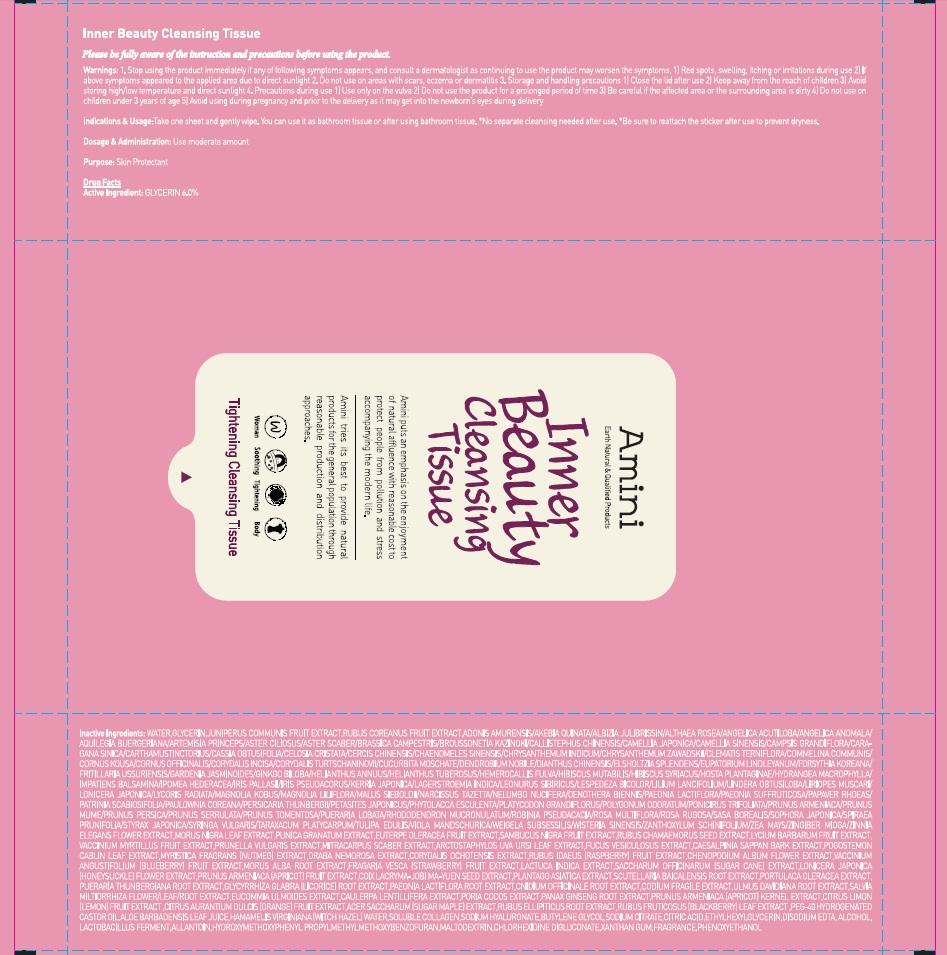 DRUG LABEL: Inner Beauty Cleansing Tissue
NDC: 70220-020 | Form: SOLUTION
Manufacturer: AMINI
Category: otc | Type: HUMAN OTC DRUG LABEL
Date: 20151123

ACTIVE INGREDIENTS: GLYCERIN 6.0 g/100 g
INACTIVE INGREDIENTS: WATER; JUNIPERUS COMMUNIS FRUIT

ACTIVE INGREDIENT

Active Ingredient: GLYCERIN 6.0%

INACTIVE INGREDIENT

Inactive Ingredients: WATER,JUNIPERUS COMMUNIS FRUIT EXTRACT,RUBUS COREANUS FRUIT EXTRACT,ADONIS AMURENSIS/AKEBIA QUINATA/ALBIZIA JULIBRISSIN/ALTHAEA ROSEA/ANGELICA ACUTILOBA/ANGELICA ANOMALA/AQUILEGIA BUERGERIANA/ARTEMISIA PRINCEPS/ASTER CILIOSUS/ASTER SCABER/BRASSICA CAMPESTRIS/BROUSSONETIA KAZINOKI/CALLISTEPHUS CHINENSIS/CAMELLIA JAPONICA/CAMELLIA SINENSIS/CAMPSIS GRANDIFLORA/CARAGANA SINICA/CARTHAMUSTINCTORIUS/CASSIA OBTUSIFOLIA/CELOSIA CRISTATA/CERCIS CHINENSIS/CHAENOMELES SINENSIS/CHRYSANTHEMUM INDICUM/CHRYSANTHEMUM ZAWADSKII/CLEMATIS TERNIFLORA/COMMELINA COMMUNIS/CORNUS KOUSA/CORNUS OFFICINALIS/CORYDALIS INCISA/CORYDALIS TURTSCHANINOVII/CUCURBITA MOSCHATE/DENDROBIUM NOBILE/DIANTHUS CHINENSIS/ELSHOLTZIA SPLENDENS/EUPATORIUM LINDLEYANUM/FORSYTHIA KOREANA/FRITILLARIA USSURIENSIS/GARDENIA JASMINOIDES/GINKGO BILOBA/HELIANTHUS ANNUUS/HELIANTHUS TUBEROSUS/HEMEROCALLIS FULVA/HIBISCUS MUTABILIS/HIBISCUS SYRIACUS/HOSTA PLANTAGINAE/HYDRANGEA MACROPHYLLA/IMPATIENS BALSAMINA/IPOMEA HEDERACEA/IRIS PALLASII/IRIS PSEUDACORUS/KERRIA JAPONICA/LAGERSTROEMIA INDICA/LEONURUS SIBIRICUS/LESPEDEZA BICOLOR/LILIUM LANCIFOLIUM/LINDERA OBTUSILOBA/LIRIOPES MUSCARI/LONICERA JAPONICA/LYCORIS RADIATA/MAGNOLIA KOBUS/MAGNOLIA LILIFLORA/MALUS SIEBOLDII/NARCISSUS TAZETTA/NELUMBO NUCIFERA/OENOTHERA BIENNIS/PAEONIA LACTIFLORA/PAEONIA SUFFRUTICOSA/PAPAVER RHOEAS/PATRINIA SCABIOSIFOLIA/PAULOWNIA COREANA/PERSICARIA THUNBERGII/PETASITES JAPONICUS/PHYTOLACCA ESCULENTA/PLATYCODON GRANDIFLORUS/POLYGONUM ODORATUM/PONICIRUS TRIFOLIATA/PRUNUS ARMENIACA/PRUNUS MUME/PRUNUS PERSICA/PRUNUS SERRULATA/PRUNUS TOMENTOSA/PUERARIA LOBATA/RHODODENDRON MUCRONULATUM/ROBINIA PSEUDACACIA/ROSA MULTIFLORA/ROSA RUGOSA/SASA BOREALIS/SOPHORA JAPONICA/SPIRAEA PRUNIFOLIA/STYRAX JAPONICA/SYRINGA VULGARIS/TARAXACUM PLATYCARPUM/TULIPA EDULIS/VIOLA MANDSCHURICA/WEIGELA SUBSESSILIS/WISTERIA SINENSIS/ZANTHOXYLUM SCHINIFOLIUM/ZEA MAYS/ZINGIBER MIOGA/ZINNIA ELEGANS FLOWER EXTRACT,MORUS NIGRA LEAF EXTRACT,PUNICA GRANATUM EXTRACT,EUTERPE OLERACEA FRUIT EXTRACT,SAMBUCUS NIGRA FRUIT EXTRACT,RUBUS CHAMAEMORUS SEED EXTRACT,LYCIUM BARBARUM FRUIT EXTRACT,VACCINIUM MYRTILLUS FRUIT EXTRACT,PRUNELLA VULGARIS EXTRACT,MITRACARPUS SCABER EXTRACT,ARCTOSTAPHYLOS UVA URSI LEAF EXTRACT,FUCUS VESICULOSUS EXTRACT,CAESALPINIA SAPPAN BARK EXTRACT,POGOSTEMON CABLIN LEAF EXTRACT,MYRISTICA FRAGRANS (NUTMEG) EXTRACT,DRABA NEMOROSA EXTRACT,CORYDALIS OCHOTENSIS EXTRACT,RUBUS IDAEUS (RASPBERRY) FRUIT EXTRACT,CHENOPODIUM ALBUM FLOWER EXTRACT,VACCINIUM ANGUSTIFOLIUM (BLUEBERRY) FRUIT EXTRACT,MORUS ALBA ROOT EXTRACT,FRAGARIA VESCA (STRAWBERRY) FRUIT EXTRACT,LACTUCA INDICA EXTRACT,SACCHARUM OFFICINARUM (SUGAR CANE) EXTRACT,LONICERA JAPONICA (HONEYSUCKLE) FLOWER EXTRACT,PRUNUS ARMENIACA (APRICOT) FRUIT EXTRACT,COIX LACRYMA-JOBI MA-YUEN SEED EXTRACT,PLANTAGO ASIATICA EXTRACT,SCUTELLARIA BAICALENSIS ROOT EXTRACT,PORTULACA OLERACEA EXTRACT,PUERARIA THUNBERGIANA ROOT EXTRACT,GLYCYRRHIZA GLABRA (LICORICE) ROOT EXTRACT,PAEONIA LACTIFLORA ROOT EXTRACT,CNIDIUM OFFICINALE ROOT EXTRACT,CODIUM FRAGILE EXTRACT,ULMUS DAVIDIANA ROOT EXTRACT,SALVIA MILTIORRHIZA FLOWER/LEAF/ROOT EXTRACT,EUCOMMIA ULMOIDES EXTRACT,CAULERPA LENTILLIFERA EXTRACT,PORIA COCOS EXTRACT,PANAX GINSENG ROOT EXTRACT,PRUNUS ARMENIACA (APRICOT) KERNEL EXTRACT,CITRUS LIMON (LEMON) FRUIT EXTRACT ,CITRUS AURANTIUM DULCIS (ORANGE) FRUIT EXTRACT,ACER SACCHARUM (SUGAR MAPLE) EXTRACT,RUBUS ELLIPITICUS ROOT EXTRACT,RUBUS FRUTICOSUS (BLACKBERRY) LEAF EXTRACT ,PEG-40 HYDROGENATED CASTOR OIL,ALOE BARBADENSIS LEAF JUICE,HAMAMELIS VIRGINIANA (WITCH HAZEL) WATER,SOLUBLE COLLAGEN,SODIUM HYALURONATE,BUTYLENE GLYCOL,SODIUM CITRATE,CITRIC ACID,ETHYLHEXYLGLYCERIN,DISODIUM EDTA,ALCOHOL,LACTOBACILLUS FERMENT,ALLANTOIN,HYDROXYMETHOXYPHENYL PROPYLMETHYLMETHOXYBENZOFURAN,MALTODEXTRIN,CHLORHEXIDINE DIGLUCONATE,XANTHAN GUM,FRAGRANCE,PHENOXYETHANOL

PURPOSE

Purpose: Skin Protectant

WARNINGS

Warnings: 1. Stop using the product immediately if any of following symptoms appears, and consult a dermatologist as continuing to use the product may worsen the symptoms. 1) Red spots, swelling, itching or irritations during use 2) If above symptoms appeared to the applied area due to direct sunlight 2. Do not use on areas with scars, eczema or dermatitis 3. Storage and handling precautions 1) Close the lid after use 2) Keep away from the reach of children 3) Avoid storing high/low temperature and direct sunlight 4. Precautions during use 1) Use only on the vulva 2) Do not use the product for a prolonged period of time 3) Be careful if the affected area or the surrounding area is dirty 4) Do not use on children under 3 years of age 5) Avoid using during pregnancy and prior to the delivery as it may get into the newborn’s eyes during delivery

KEEP OUT OF REACH OF CHILDREN

Keep away from the reach of children

INDICATIONS & USAGE

Indications & Usage: Take one sheet and gently wipe. You can use it as bathroom tissue or after using bathroom tissue. *No separate cleansing needed after use. *Be sure to reattach the sticker after use to prevent dryness.

DOSAGE & ADMINISTRATION

Dosage & Administration: Use moderate amount.